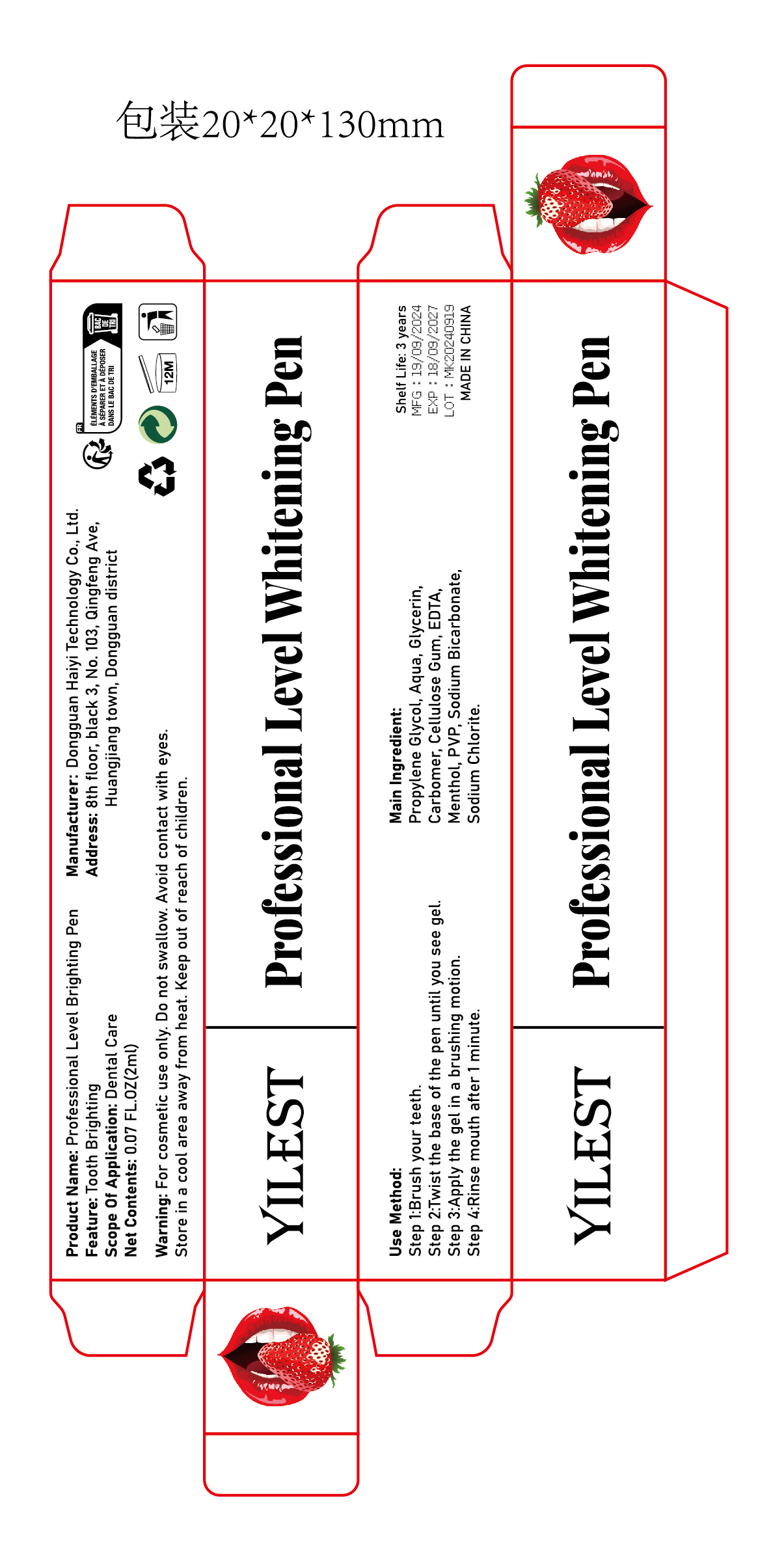 DRUG LABEL: Professional Level Brighting Pen
NDC: 84732-087 | Form: LIQUID
Manufacturer: Dongguan Haiyi Technology Co.,Ltd.
Category: otc | Type: HUMAN OTC DRUG LABEL
Date: 20241106

ACTIVE INGREDIENTS: DIPROPYLENE GLYCOL 1 mg/100 mL
INACTIVE INGREDIENTS: MENTHOL; PVP; SODIUM CHLORITE; WATER; SODIUM BICARBONATE; EDTA; CELLULOSE GUM; GLYCERIN; CARBOMER

Active ingredient

Propylene Glycol

Inactive ingredient

Aqua, Glycerin,Carbomer, Cellulose Gum, EDTA,Menthol, PVP, Sodium Bicarbonate,Sodium Chlorite.

Purpose section

Tooth Brighting

Warning

For cosmetic use only.

Do not swallow. Avoid contact with eyes.
Store in a cool area away from heat.

Keep out of reach of children.

stop use

This product may cause allergic reactions in asmall number of people.
lf youexperience any discomfort,please stop using it immediately.

not use

Not suitable for use by children, pregnantor breast feeding people.

OUT OF CHILDREN

KEEP THE PRODUCT OUT OF REACH OF CHILDREN to

HOW TO USE

Step 1:Brush your teeth.
Step 2:Twist the base of the pen until you see gel.
Step 3:Apply the gel in a brushing motion.
Step 4:Rinse mouth after 1 minute.

Dosage

Once a day in the morning and evening